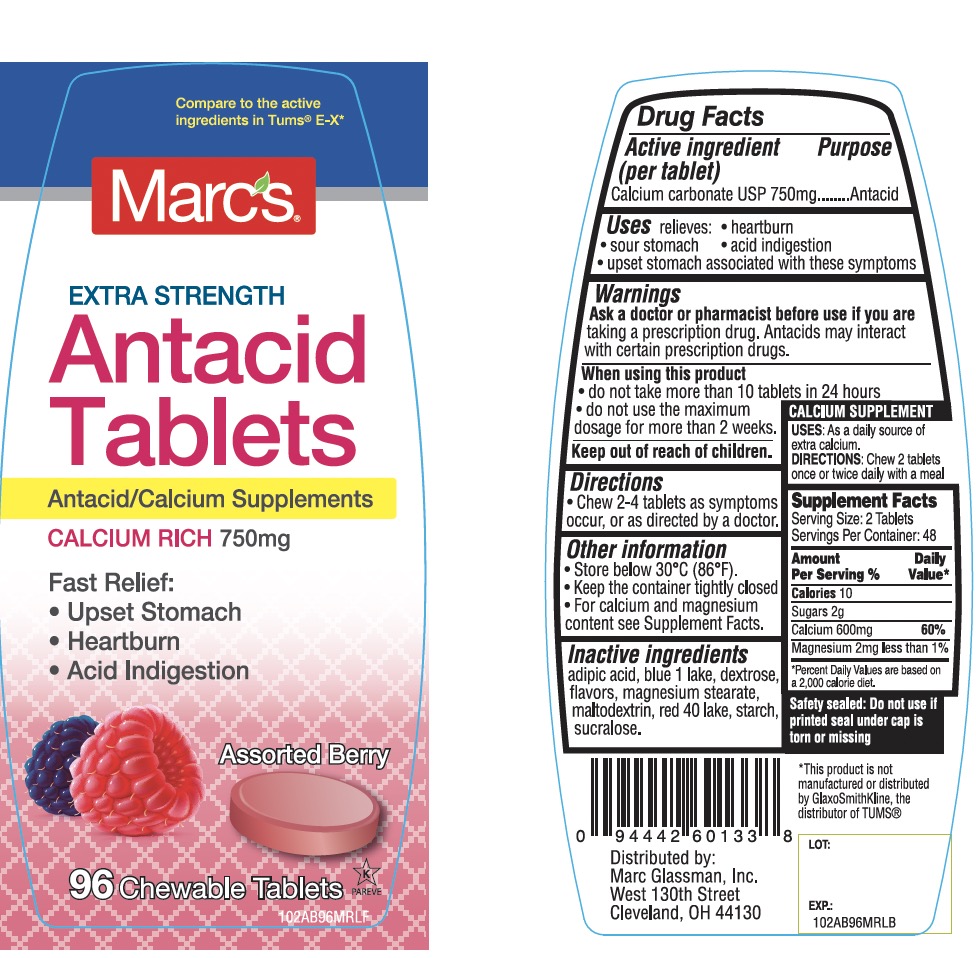 DRUG LABEL: Marc Glassman

NDC: 68998-102 | Form: TABLET, CHEWABLE
Manufacturer: MARC GLASSMAN, INC.
Category: otc | Type: HUMAN OTC DRUG LABEL
Date: 20250919

ACTIVE INGREDIENTS: CALCIUM CARBONATE 750 mg/1 1
INACTIVE INGREDIENTS: ADIPIC ACID; DEXTROSE, UNSPECIFIED FORM; FD&C BLUE NO. 1; FD&C RED NO. 40; MAGNESIUM STEARATE; MALTODEXTRIN; STARCH, CORN; SUCRALOSE

Marcs Extra Strength Antacid Calcium Drug Facts

Active ingredient (per tablet)

Calcium Carbonate USP 750mg

Purpose

Antacid

Uses

relieves

- heartburn
- acid indigestion
- sour stomach
- upset stomach associated with these symptoms

Warnings

Ask a doctor or pharmacist before use if you arepresently taking a prescription drug. Antacids may interact with certain prescription drugs.

When using this product

- do not take more than 10 tablets in 24 hours
- if pregnant do not take more than 6 tablets in 24 hours
- do not use the maximum dosage for more than 2 weeks except under the advice and supervision of a doctor.

Directions

- adults and children 12 years of age and over:chew 2-4 tablets as symptoms occur, or as directed by a doctor. Do not swallow tablets whole.
- do not take for symptoms that persist for more than 2 weeks unless advised by a doctor

Other information

- each tablets contains:elemental calcium 300mg
- Store at room temperature. Keep the container tightly closed
- Safety sealed: Do not use if printed seal under cap is torn or missing

Inactive ingredients

adipic acid, dextrose, FD&C Blue No. 1, FD&C Red No. 40, flavors, magnesium stearate, maltodextrin, starch, sucralose.

Questions?

1-866-467-2748

Package/Label Principal Display Panel

NDC # 68998-102-96

Marcs®

Compare to the active ingredient in Extra Strength Tums®

EXTRA STRENGTH

Antacid Tablets

Calcium Carbonate 750 mg

Fast Relief:

- Upset Stomach
- Heartburn
- Acid Indigestion

Assorted Berry Flavors

Naturally and Artificially Flavored

96 CHEWABLE TABLETS

GLUTEN- FREE

K PAREVE

Distributed by:

Marc Glassman, Inc.

West 130thStreet

Cleveland, OH 44130

This product is not manufactured or distributed by GlaxoSmithKline LLC, owner of the registered trademark, Extra Strength Tums®.